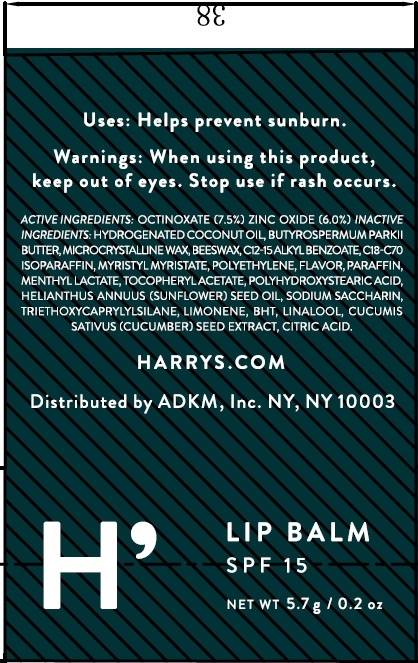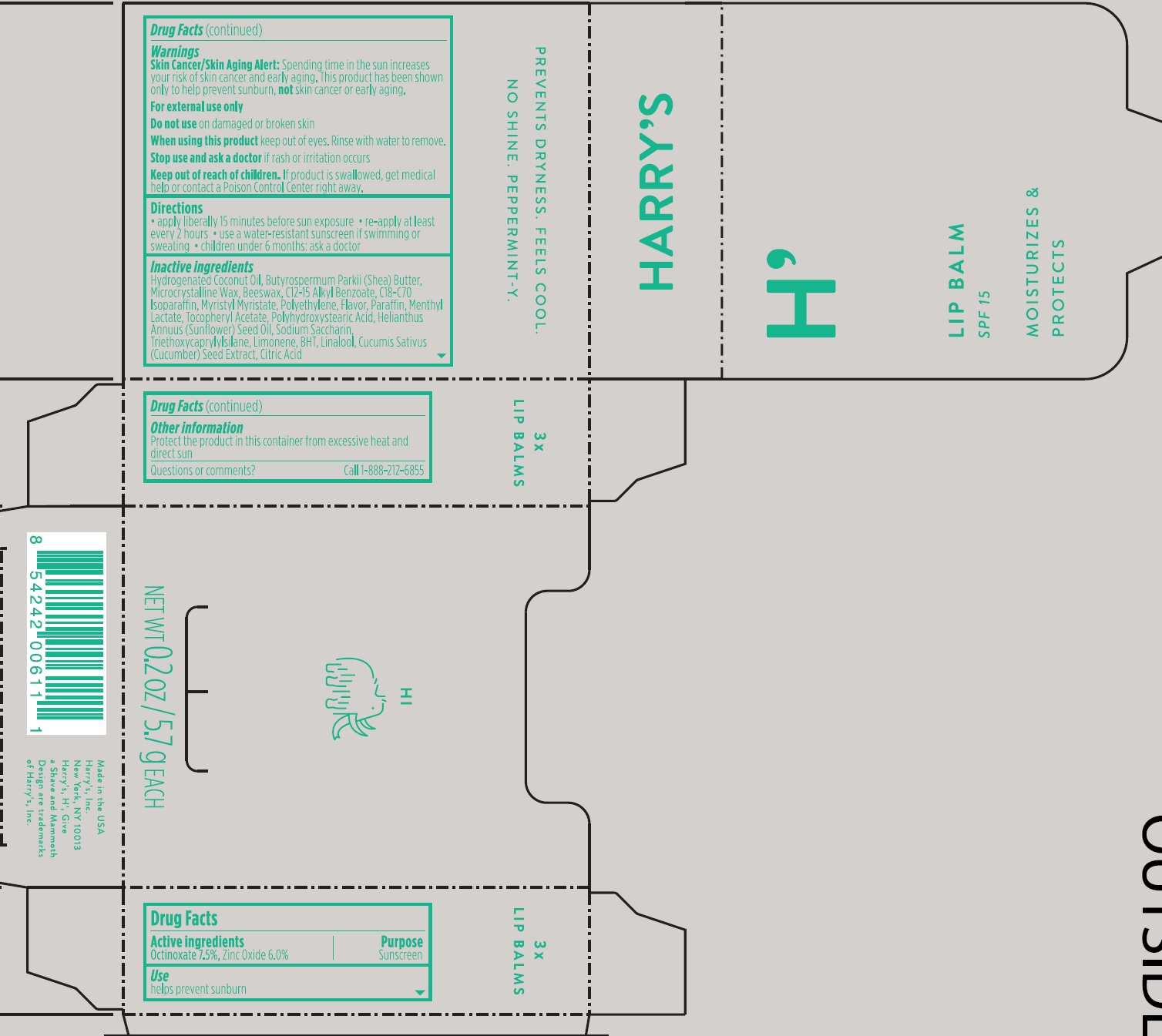 DRUG LABEL: Lip Balm SPF
NDC: 70533-002 | Form: STICK
Manufacturer: Harry's, Inc.
Category: otc | Type: HUMAN OTC DRUG LABEL
Date: 20160404

ACTIVE INGREDIENTS: OCTINOXATE 75 mg/1 g; ZINC OXIDE 60 mg/1 g
INACTIVE INGREDIENTS: HYDROGENATED COCONUT OIL; SHEA BUTTER; MICROCRYSTALLINE WAX; YELLOW WAX; ALKYL (C12-15) BENZOATE; MYRISTYL MYRISTATE; HIGH DENSITY POLYETHYLENE; METHYL SALICYLATE; PARAFFIN; MENTHYL LACTATE, (-)-; .ALPHA.-TOCOPHEROL ACETATE; POLYHYDROXYSTEARIC ACID (2300 MW); SUNFLOWER OIL; SACCHARIN SODIUM; TRIETHOXYCAPRYLYLSILANE; BUTYLATED HYDROXYTOLUENE; LINALOOL, (+/-)-; CUCUMBER SEED; CITRIC ACID MONOHYDRATE

Lip Balm SPF 15

Active ingredients

Octinoxate 7.5%

Zinc Oxide 6.0%

Purpose

Sunscreen

Use

helps prevent sunburn

Warnings

Skin Cancer/Skin Aging Alert: Spending time in the sun increases your risk of skin cancer and early aging. This product has been shown only to help prevent sunburn, not skin cancer or early aging.

For external use only

Do not use

on damaged or broken skin

When using this product

keep out of eyes. Rinse with water to remove.

Stop use and ask a doctor

if rash or irritation occurs

Keep out of reach of children.

If product is swallowed, get medical help or contact a Poison Control Center right away.

Directions

• apply liberally 15 minutes before sun exposure • re-apply at least every 2 hours • use a water-resistant sunscreen if swimming or sweating • children under 6 months: ask a doctor

Inactive ingredients

Hydrogenated Coconut Oil, Butyrospermum Parkii (Shea) Butter, Microcrystalline Wax, Beeswax, C12-15 Alkyl Benzoate, C18-C70 Isoparaffin, Myristyl Myristate, Polyethylene, Flavor, Paraffin, Menthyl Lactate, Tocopheryl Acetate, Polyhydroxystearic Acid, Helianthus Annuus (Sunflower) Seed Oil, Sodium Saccharin, Triethoxycaprylylsilane, Limonene, BHT, Linalool, Cucumis Sativus (Cucumber) Seed Extract, Citric Acid

Other information

Protect the product in this container from excessive heat and direct sun

Questions or comments?

Call 1-888-212-6855